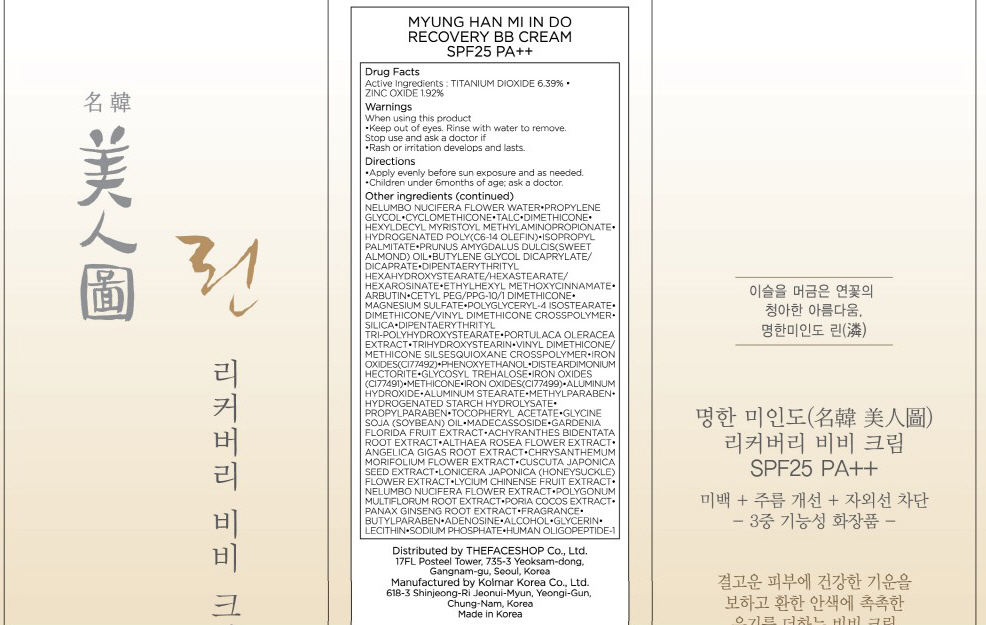 DRUG LABEL: MYUNG HAN MI IN DO RECOVERY BB
NDC: 51523-016 | Form: CREAM
Manufacturer: THEFACESHOP CO., LTD.
Category: otc | Type: HUMAN OTC DRUG LABEL
Date: 20100714

ACTIVE INGREDIENTS: TITANIUM DIOXIDE 2.87 g/45 g; ZINC OXIDE 0.86 g/45 g

Drug Facts

Active Ingredients: TITANIUM DIOXIDE, ZINC OXIDE

Inactive Ingredients:
NELUMBO NUCIFERA FLOWER WATER, PROPYLENE GLYCOL, CYCLOMETHICONE, TALC, DIMETHICONE, HEXYLDECYL MYRISTOYL METHYLAMINOPROPIONATE,
HYDROGENATED POLY(C6-14 OLEFIN), ISOPROPYL PALMITATE, PRUNUS AMYGDALUS DULCIS (SWEET ALMOND) OIL, BUTYLENE GLYCOL DICAPRYLATE/DICAPRATE,
DIPENTAERYTHRITYL HEXAHYDROXYSTEARATE/HEXASTEARATE/HEXAROSINATE, ETHYLHEXYL METHOXYCINNAMATE, ARBUTIN, CETYL PEG/PPG-10/1 DIMETHICONE, MAGNESIUM SULFATE, POLYGLYCERYL-4 ISOSTEARATE, DIMETHICONE/VINYL DIMETHICONE CROSSPOLYMER, SILICA, DIPENTAERYTHRITYL TRI-POLYHYDROXYSTEARATE, PORTULACA OLERACEA EXTRACT, TRIHYDROXYSTEARIN, VINYL DIMETHICONE/METHICONE SILSESQUIOXANE CROSSPOLYMER, IRON OXIDES(CI77492), PHENOXYETHANOL, DISTEARDIMONIUM HECTORITE, GLYCOSYL TREHALOSE, IRON OXIDES(CI77491), METHICONE, IRON OXIDES(CI77499), ALUMINUM HYDROXIDE, ALUMINUM STEARATE, METHYLPARABEN, HYDROGENATED STARCH HYDROLYSATE, PROPYLPARABEN, TOCOPHERYL ACETATE, GLYCINE SOJA (SOYBEAN) OIL, MADECASSOSIDE, GARDENIA FLORIDA FRUIT EXTRACT, ACHYRANTHES BIDENTATA ROOT EXTRACT, ALTHAEA ROSEA FLOWER EXTRACT, ANGELICA GIGAS ROOT EXTRACT, CHRYSANTHEMUM MORIFOLIUM FLOWER EXTRACT, CUSCUTA JAPONICA SEED EXTRACT, LONICERA JAPONICA (HONEYSUCKLE) FLOWER EXTRACT, LYCIUM CHINENSE FRUIT EXTRACT, NELUMBO NUCIFERA FLOWER EXTRACT, POLYGONUM MULTIFLORUM ROOT EXTRACT, PORIA COCOS EXTRACT, PANAX GINSENG ROOT EXTRACT,
FRAGRANCE, BUTYLPARABEN, ADENOSINE, ALCOHOL, GLYCERIN, LECITHIN, SODIUM PHOSPHATE, HUMAN OLIGOPEPTIDE-1

Warnings:
When using this product
Keep out of eyes. Rinse with water to remove.
Stop use and ask a doctor if
Rash or irritation develops and lasts.
Directions:
Apply evenly before sun exposure and as needed.
Children under 6months of age; ask a doctor.